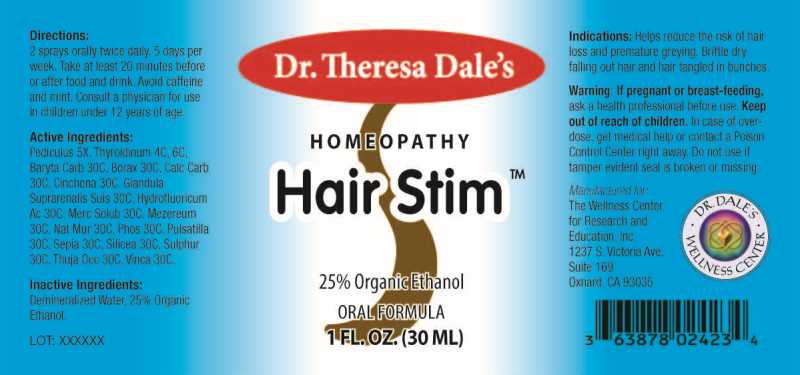 DRUG LABEL: HAIR STIM
NDC: 50181-0081 | Form: LIQUID
Manufacturer: The Wellness Center for Research and Education, Inc.
Category: homeopathic | Type: HUMAN OTC DRUG LABEL
Date: 20250606

ACTIVE INGREDIENTS: PEDICULUS HUMANUS VAR. CAPITIS 5 [hp_X]/1 mL; THYROID 4 [hp_C]/1 mL; BARIUM CARBONATE 30 [hp_C]/1 mL; SODIUM BORATE 30 [hp_C]/1 mL; OYSTER SHELL CALCIUM CARBONATE, CRUDE 30 [hp_C]/1 mL; CINCHONA OFFICINALIS BARK 30 [hp_C]/1 mL; SUS SCROFA ADRENAL GLAND 30 [hp_C]/1 mL; HYDROFLUORIC ACID 30 [hp_C]/1 mL; MERCURIUS SOLUBILIS 30 [hp_C]/1 mL; DAPHNE MEZEREUM BARK 30 [hp_C]/1 mL; SODIUM CHLORIDE 30 [hp_C]/1 mL; PHOSPHORUS 30 [hp_C]/1 mL; PULSATILLA PRATENSIS WHOLE 30 [hp_C]/1 mL; SEPIA OFFICINALIS JUICE 30 [hp_C]/1 mL; SILICON DIOXIDE 30 [hp_C]/1 mL; SULFUR 30 [hp_C]/1 mL; THUJA OCCIDENTALIS LEAFY TWIG 30 [hp_C]/1 mL; PERVINCA MINOR WHOLE 30 [hp_C]/1 mL
INACTIVE INGREDIENTS: WATER; ALCOHOL

DRUG FACTS:

ACTIVE INGREDIENTS:

Pediculus Capitis 5X, Thyroidinum (Suis) 4C, 6C, Baryta Carbonica 30C, Borax 30C, Calcarea Carbonica 30C, Cinchona Officinalis 30C, Glandula Suprarenalis Suis 30C, Hydrofluoricum Acidum 30C, Mercurius Solubilis 30C, Mezereum 30C, Natrum Muriaticum 30C, Phosphorus 30C, Pulsatilla (Pratensis) 30C, Sepia 30C, Silicea 30C, Sulphur 30C, Thuja Occidentalis 30C, Vinca Minor

INDICATIONS:

Helps reduce the risk of hair loss and premature greying. Brittle, dry, falling out hair and hair tangled in bunches.

WARNINGS:

If pregnant or breast-feeding, ask a health professional before use.

Keep out of reach of children. In case of overdose, get medical help or contact a Poison Control Center right away.

Do not use if tamper evident seal is broken or missing.

Keep out of reach of children. In case of overdose, get medical help or contact a Poison Control Center right away.

DIRECTIONS

2 sprays orally twice daily, 5 days per week. Take at least 20 minutes before or after food and drink. Avoid caffeine and mint. Consult a physician for use in children under 12 years of age.

INDICATIONS:

Helps reduce the risk of hair loss and premature greying. Brittle, dry, falling out hair and hair tangled in bunches.

INACTIVE INGREDIENTS:

Demineralized Water, 25% Ethanol

QUESTIONS:

Manufactured for:

The Wellness Center

for Research and

Education, Inc.

1237 S. Victoria Ave.

Suite. 169

Oxnard, CA 93035

PACKAGE LABEL DISPLAY:

Dr. Theresa Dale's

HOMEOPATHY

Hair Stim

ORAL FORMULA

1 FL. OZ. (30 ML)